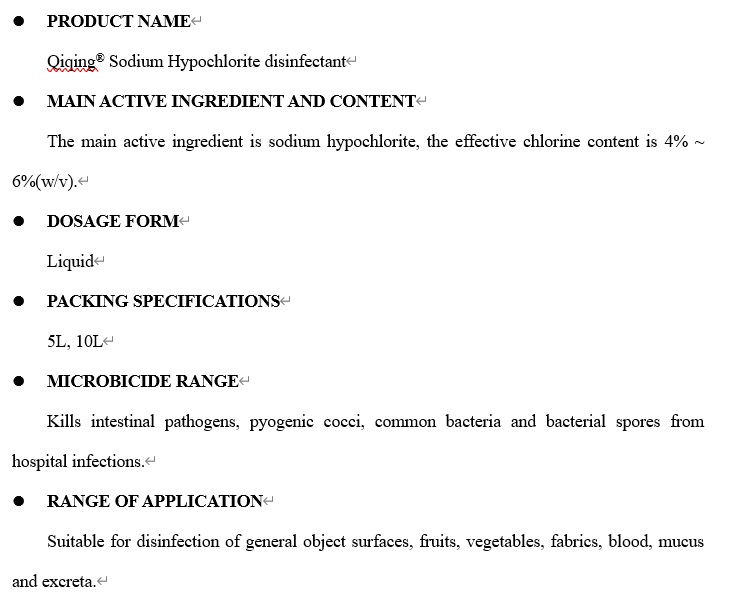 DRUG LABEL: (Qiqing) Sodium Hypochlorite Disinfectant
NDC: 77919-003 | Form: LIQUID
Manufacturer: Qingdao precision medical technology co., LTD. Zibo branch
Category: otc | Type: HUMAN OTC DRUG LABEL
Date: 20200621

ACTIVE INGREDIENTS: SODIUM HYPOCHLORITE 6 g/100 mL
INACTIVE INGREDIENTS: WATER

Sodium Hypochlorite Disinfectant

Active Ingredient(s)

Sodium hypochlorite 4% ~ 6%(w/v)

Purpose

Antimicrobial

Use

Suitable for disinfection of general object surfaces, fruits, vegetables, fabrics, blood, mucus and excreta.

Warnings

This product is a topical disinfectant and cannot be mixed with other disinfection products.

It’s recommended to wear gloves and avoid contact with the skin during use. If the original solution comes in contact with the skin, rinse it with water; if it gets in eyes, immediately rinse it with water.

Don’t dilute with hot water above 40 ℃.

Corrosive to metals and bleaching to fabrics.

It’s normal to have a few floating objects and sediments, and you can continue to use them.

Store in a closed, dark, cool and dry place. Use it as soon as possible after opening.

When using this product keep out of eyes, ears, and mouth. In case of contact with eyes, rinse eyes thoroughly with water.
Stop use and ask a doctor if irritation or rash occurs. These may be signs of a serious condition.
Keep out of reach of children. If swallowed, get medical help or contact a Poison Control Center right away.

Keep out of reach of children. If swallowed, get medical help or contact a Poison Control Center right away.

Directions

- Place enough product on hands to cover all surfaces. Rub hands together until dry.
- Supervise children under 6 years of age when using this product to avoid swallowing.

Other information

- Store between 15-30C (59-86F)
- Avoid freezing and excessive heat above 40C (104F)

Inactive ingredients

Water

Package Label - Principal Display Panel

PRODUCT NAME

Qiqing® Sodium Hypochlorite disinfectant

MAIN ACTIVE INGREDIENT AND CONTENT

The main active ingredient is sodium hypochlorite, the effective chlorine content is 4% ~ 6%(w/v).

DOSAGE FORM

Liquid

PACKING SPECIFICATIONS

5L, 10L

MICROBICIDE RANGE

Kills intestinal pathogens, pyogenic cocci, common bacteria and bacterial spores from hospital infections.